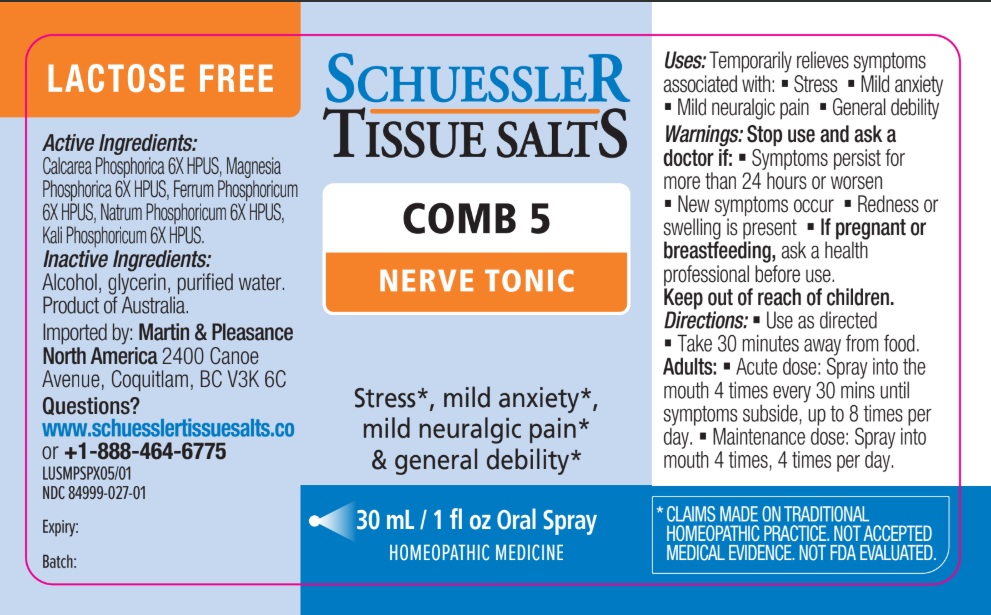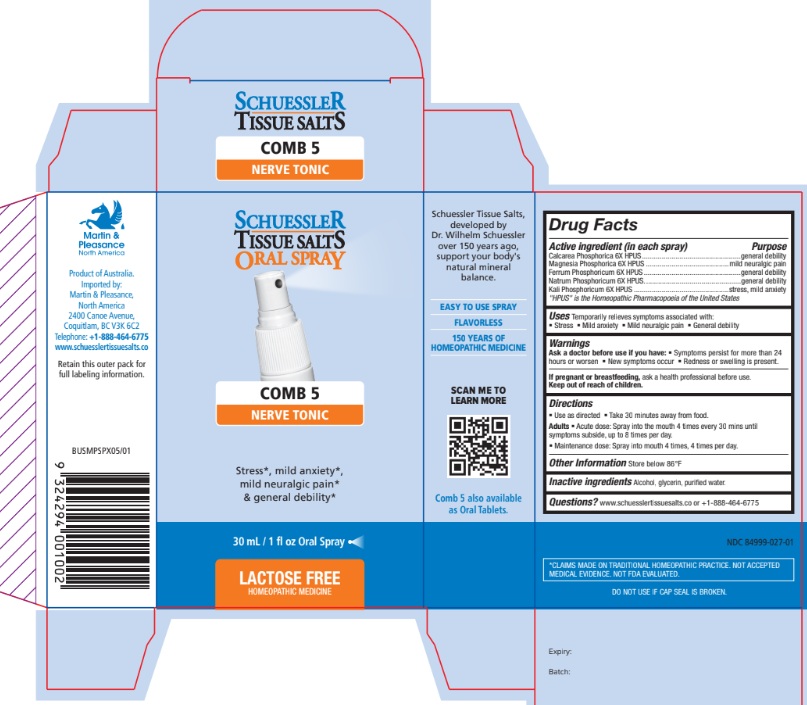 DRUG LABEL: Schuessler Tissue Salts Comb 5 Nerve Tonic
NDC: 84999-027 | Form: SPRAY
Manufacturer: Martin & Pleasance Pty Ltd
Category: homeopathic | Type: HUMAN OTC DRUG LABEL
Date: 20250813

ACTIVE INGREDIENTS: TRIBASIC CALCIUM PHOSPHATE 6 [hp_X]/30 mL; MAGNESIUM PHOSPHATE, DIBASIC 6 [hp_X]/30 mL; FERROUS PHOSPHATE 6 [hp_X]/30 mL; SODIUM PHOSPHATE, DIBASIC, ANHYDROUS 6 [hp_X]/30 mL; DIBASIC POTASSIUM PHOSPHATE 6 [hp_X]/30 mL
INACTIVE INGREDIENTS: ALCOHOL; GLYCERIN; WATER

Active ingredient (in each spray) Purpose

Calcarea Phosphorica 6X HPUS .................................................. general debility
Magnesia Phosphorica 6X HPUS .......................................... mild neuralgic pain
Ferrum Phosphoricum 6X HPUS ................................................. general debility
Natrum Phosphoricum 6X HPUS ................................................. general debility
Kali Phosphoricum 6X HPUS ................................................ stress, mild anxiety

"HPUS" is the Homeopathic Pharmacopoeia of the United States

Uses

Temporarily relieves symptoms associated with:

- Stress
- Mild anxiety
- Mild neuralgic pain
- General debility

Warnings

Ask a doctor before use if you have:

- Symptoms persist for more than 24 hours or worsen
- New symptoms occur
- Redness or swelling is present.

If pregnant or breastfeeding, ask a health professional before use. Keep out of reach of children.

Directions

- Use as directed
- Take 30 minutes away from food.

Adults

- Acute dose: Spray into the mouth 4 times every 30 mins until symptoms subside, up to 8 times per day.
- Maintenance dose: Spray into mouth 4 times, 4 times per day.

Other Information

Store below 86°F

Inactive Ingredients

Alcohol, Glycerin, Purified Water

Questions?www.schuesslertissuesalts.co or + 1-888-464-6775